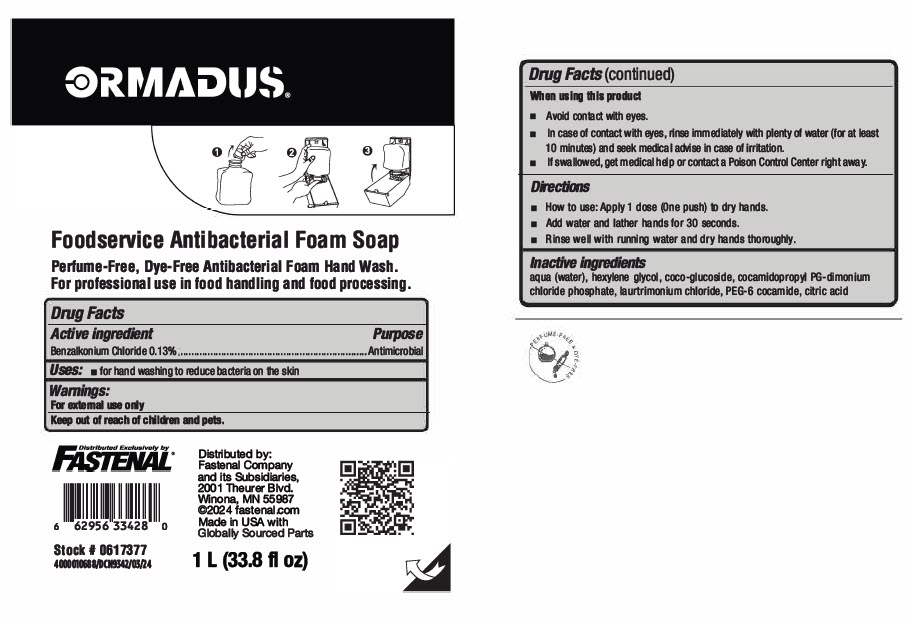 DRUG LABEL: Ormadus Foodservice Antibacterial Foam
NDC: 11084-023 | Form: LIQUID
Manufacturer: SC Johnson Professional USA Inc
Category: otc | Type: HUMAN OTC DRUG LABEL
Date: 20250107

ACTIVE INGREDIENTS: BENZALKONIUM CHLORIDE 0.13 g/100 mL
INACTIVE INGREDIENTS: WATER; HEXYLENE GLYCOL; COCO-GLUCOSIDE; LAURTRIMONIUM CHLORIDE; PEG-6 COCAMIDE; ANHYDROUS CITRIC ACID

Ormadus® Foodservice Antibacterial Foam Soap

Drug Facts

Active ingredient

Benzalkonium Chloride 0.13%

Purpose

Antimicrobial

Uses

- for hand washing to reduce bacteria on the skin

Warnings

For external use only

Keep out of reach of children and pets.

When using this product

- Avoid contact with eyes.
- In case of contact with eyes, rinse immediately with plenty of water (for at least 10 minutes) and seek medical advise in case of irritation.
- If swallowed, get medical help or contact a Poison Control Center right away.

Directions

- How to use: Apply 1 dose (One push) to dry hands.
- Add water and lather hands for 30 seconds.
- Rinse well with running water and dry hands thoroughly.

Inactive ingredients

aqua (water), hexylene glycol, coco-glucoside, cocamidopropyl PG-dimonium chloride phosphate, laurtrimonium chloride, PEG-6 cocamide, citric acid

Distributed by:
Fastenal Company
and its Subsidiaries,
2001 Theurer Blvd.
Winona, MN 55987

PRINCIPAL DISPLAY PANEL - 1 L Cartridge Label

ORMADUS®

Foodservice Antibacterial Foam Soap

Perfume-Free, Dye-Free Antibacterial Foam Hand Wash.
For professional use in food handling and food processing.

Distributed Exlusively by
FASTENAL®

Stock # 0617377
4000010688/DCN9342/03/24

Distributed by:
Fastenal Company
and its Subsidiaries,
2001 Theurer Blvd.
Winona, MN 55987
©2024 fastenal.com
Made in USA with
Globally Sourced Parts

1 L (33.8 fl oz)